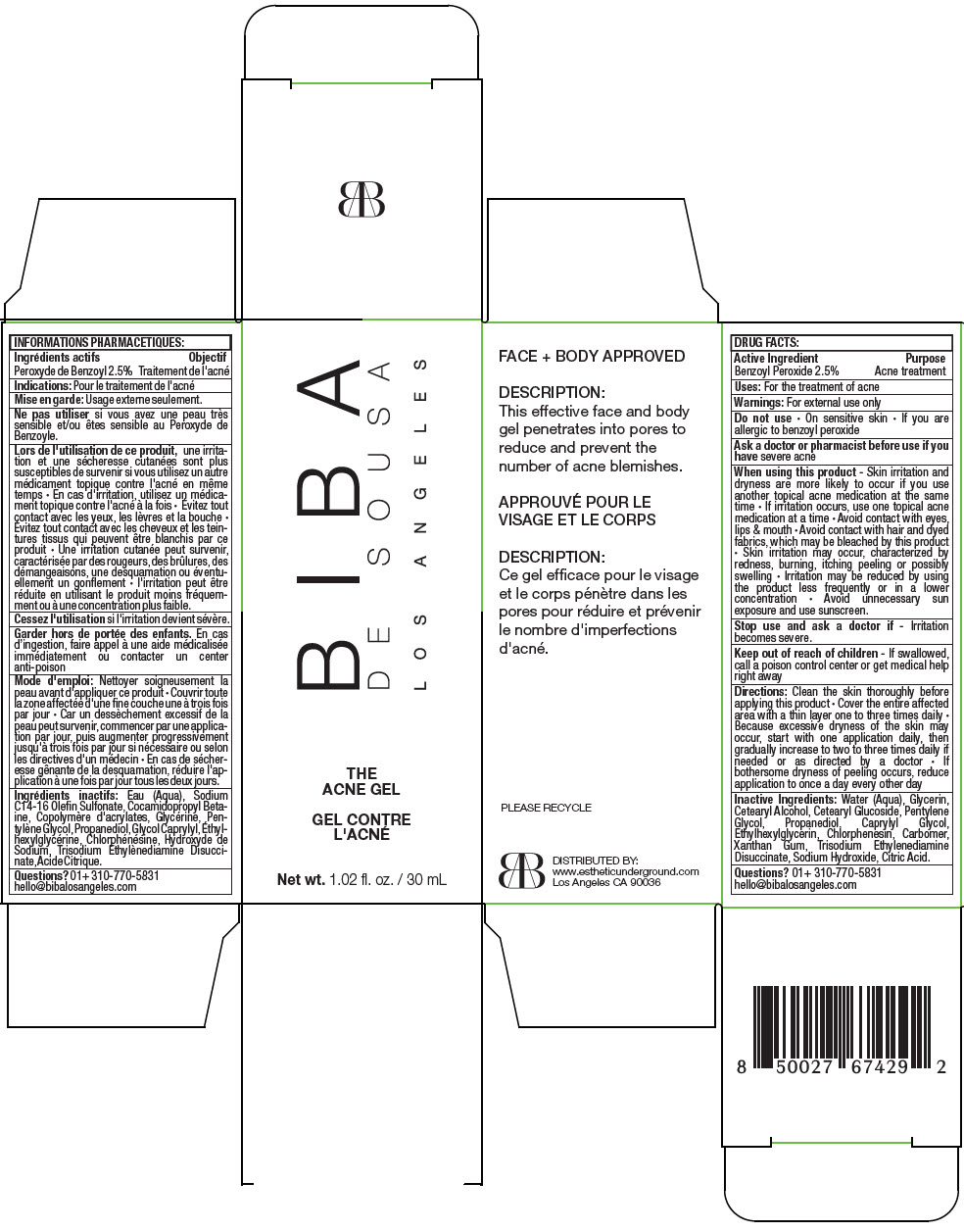 DRUG LABEL: Biba Acne
NDC: 83834-001 | Form: GEL
Manufacturer: Esthetic Underground, Inc.
Category: otc | Type: HUMAN OTC DRUG LABEL
Date: 20250307

ACTIVE INGREDIENTS: BENZOYL PEROXIDE 2.5 g/100 mL
INACTIVE INGREDIENTS: WATER 89.162 g/100 mL; GLYCERIN 3 g/100 mL; CETOSTEARYL ALCOHOL 2.8 g/100 mL; CETEARYL GLUCOSIDE 0.7 g/100 mL; PENTYLENE GLYCOL 0.35 g/100 mL; CARBOMER HOMOPOLYMER, UNSPECIFIED TYPE 0.3 g/100 mL; PROPANEDIOL 0.3 g/100 mL; XANTHAN GUM 0.3 g/100 mL; CAPRYLYL GLYCOL 0.15 g/100 mL; CHLORPHENESIN 0.15 g/100 mL; CITRIC ACID MONOHYDRATE 0.1 g/100 mL; TRISODIUM ETHYLENEDIAMINE DISUCCINATE 0.074 g/100 mL; SODIUM HYDROXIDE 0.064 g/100 mL; ETHYLHEXYLGLYCERIN 0.05 g/100 mL

Biba Acne

DRUG FACTS:

Active Ingredient

Benzoyl Peroxide 2.5%

Purpose

Acne treatment

Uses

For the treatment of acne

Warnings

For external use only

Do not use

- On sensitive skin
- If you are allergic to benzoyl peroxide

Ask a doctor or pharmacist before use if you havesevere acne

When using this product

Skin irritation and dryness are more likely to occur if you use another topical acne medication at the same time

- If irritation occurs, use one topical acne medication at a time
- Avoid contact with eyes, lips & mouth
- Avoid contact with hair and dyed fabrics, which may be bleached by this product
- Skin irritation may occur, characterized by redness, burning, itching peeling or possibly swelling
- Irritation may be reduced by using the product less frequently or in a lower concentration
- Avoid unnecessary sun exposure and use sunscreen.

Stop use and ask a doctor if

Irritation becomes severe.

Keep out of reach of children

If swallowed, call a poison control center or get medical help right away

Directions

Clean the skin thoroughly before applying this product

- Cover the entire affected area with a thin layer one to three times daily
- Because excessive dryness of the skin may occur, start with one application daily, then gradually increase to two to three times daily if needed or as directed by a doctor
- If bothersome dryness of peeling occurs, reduce application to once a day every other day

Inactive Ingredients

Water (Aqua), Glycerin, Cetearyl Alcohol, Cetearyl Glucoside, Pentylene Glycol, Propanediol, Caprylyl Glycol, Ethylhexylglycerin, Chlorphenesin, Carbomer, Xanthan Gum, Trisodium Ethylenediamine Disuccinate, Sodium Hydroxide, Citric Acid.

Questions?

01+ 310-770-5831

hello@bibalosangeles.com

DISTRIBUTED BY:
www.estheticunderground.com
Los Angeles CA 90036

PRINCIPAL DISPLAY PANEL - 30 mL Bottle Carton

BIBA
DE SOUSA
LOS ANGELES

THE
ACNE GEL

Net wt. 1.02 fl. oz. / 30 mL